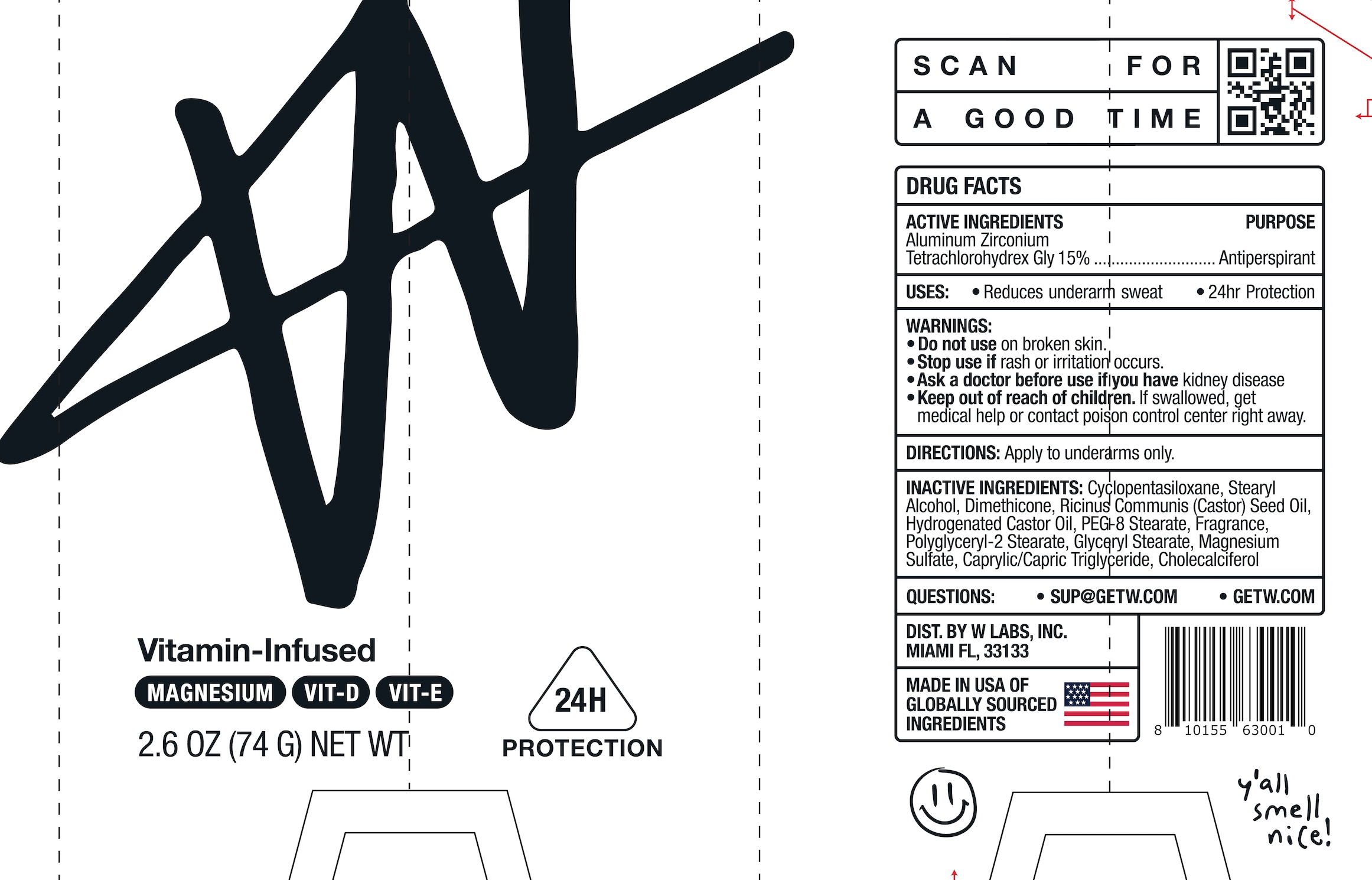 DRUG LABEL: W Fresh Ice Deodorant
NDC: 84759-101 | Form: STICK
Manufacturer: W Labs Inc
Category: otc | Type: HUMAN OTC DRUG LABEL
Date: 20241108

ACTIVE INGREDIENTS: ALUMINUM ZIRCONIUM TETRACHLOROHYDREX GLY 15 g/100 g
INACTIVE INGREDIENTS: CAPRYLIC/CAPRIC TRIGLYCERIDE; CHOLECALCIFEROL; STEARYL ALCOHOL; RICINUS COMMUNIS (CASTOR) SEED OIL; MAGNESIUM SULFATE; PEG-8 STEARATE; HYDROGENATED CASTOR OIL; CYCLOPENTASILOXANE; GLYCERYL STEARATE; POLYGLYCERYL-2 STEARATE; DIMETHICONE

W Fresh Ice Deodorant

Active ingredients

Aluminum Zirconium Tetrachlorohydrex Gly 15%

Purpose

Antiperspirant

Uses

Reduces underarm sweat
24hr protection

Warnings

Do not use

on broken skin

Stop use if

rash or irritation occurs

Ask a doctor before use if you have

kidney disease

Keep out of reach of children.

If swallowed, get medical help or contact poison control center right away

Directions

Apply to underarms only

Inactive ingredients

Cyclopentasiloxane, Stearyl Alcohol, Dimethicone, Ricinus Communis (Castor) Seed Oil, Hydrogenated Castor Oil, PEG-8 Stearate, Fragrance, Polyglyceryl-2 Stearate, Glyceryl Stearate, Magnesium Sulfate, Caprylic/Capric Triglyceride, Cholecalciferol

Questions?

SUP@GETW.COM
GETW.COM